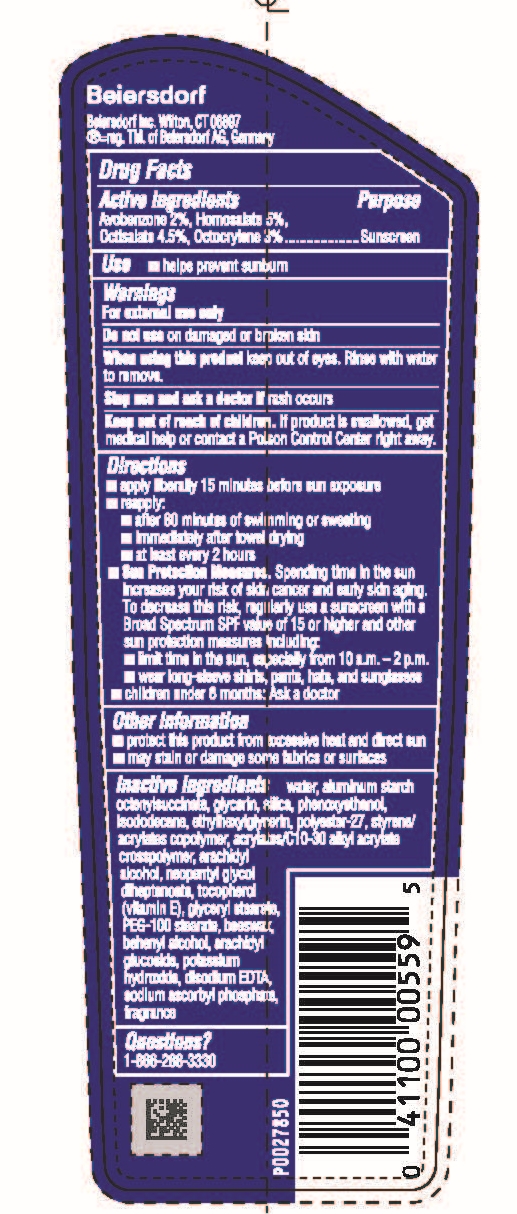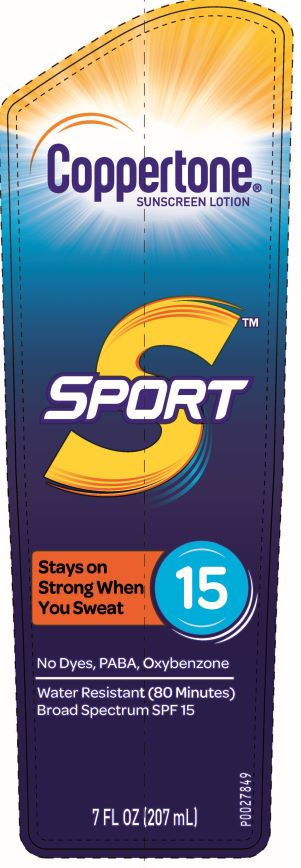 DRUG LABEL: Coppertone Sport Sunscreen SPL 15
NDC: 66800-3091 | Form: LOTION
Manufacturer: Beiersdorf Inc
Category: otc | Type: HUMAN OTC DRUG LABEL
Date: 20251231

ACTIVE INGREDIENTS: HOMOSALATE 5 g/100 g; OCTOCRYLENE 3 g/100 g; OCTISALATE 4.5 g/100 g; AVOBENZONE 2 g/100 g
INACTIVE INGREDIENTS: STYRENE/ACRYLAMIDE COPOLYMER (MW 500000); BUTYLENE GLYCOL; FRAGRANCE FLORAL ORC0902236; CARBOMER INTERPOLYMER TYPE A (55000 CPS); TOCOPHEROL; BENZYL ALCOHOL; WATER; VITAMIN A PALMITATE; OLETH-3; DISODIUM EDTA-COPPER; BUTYLOCTYL SALICYLATE; TROLAMINE; DIETHYLHEXYL SYRINGYLIDENEMALONATE; SODIUM ASCORBYL PHOSPHATE; CHLORPHENESIN

Sport Lotion SPF 15

Active ingredients

Avobenzone 2%, Homosalate 5%, Octisalate 4.5%, Octocrylene 3%

Purpose

Sunscreen

Use

■ helps prevent sunburn

Warnings

For external use only

Do not useon damaged or broken skin

WHEN USING

When using this productkeep out of eyes. Rinse with water to remove.

Stop use and ask a doctor ifrash occurs

Keep out of reach of children.If product is swallowed, get medical help or contact a Poison Control Center right away.

Directions

■ apply liberally 15 minutes before sun exposure

■ reapply:

■ after 80 minutes of swimming or sweating

■ immediately after towel drying

■ at least every 2 hours

■ Sun Protection Measures.Spending time in the sun increases your risk of skin cancer and early skin aging. To decrease this risk, regularly use a sunscreen with a Broad Spectrum SPF value of 15 or higher and other sun protection measures including:

■ limit time in the sun, especially from 10 a.m. – 2 p.m.

■ wear long-sleeve shirts, pants, hats, and sunglasses

■ children under 6 months: Ask a doctor

Other information

■ protect this product from excessive heat and direct sun

■ may stain or damage some fabrics or surfaces

Inactive ingredients

water, aluminum starch octenylsuccinate, glycerin, silica, phenoxyethanol, isododecane, ethylhexylglycerin, polyester-27, styrene/acrylates copolymer, acrylates/C10-30 alkyl acrylate crosspolymer, arachidyl alcohol, neopentyl glycol diheptanoate, tocopherol (vitamin E), glyceryl stearate, PEG-100 stearate, beeswax, behenyl alcohol, arachidyl glucoside, potassium hydroxide, disodium EDTA, sodium ascorbyl phosphate, fragrance

Questions?

1-866-288-3330

PACKAGE LABEL

Coppertone®Sunscreen Lotion

Sport 15

Stays on Strong When You Sweat

No Dyes, PABA, Oxybenzone

Water Resistant (80 Minutes)

Broad Spectrum SPF 15

7 FL OZ (207 mL)